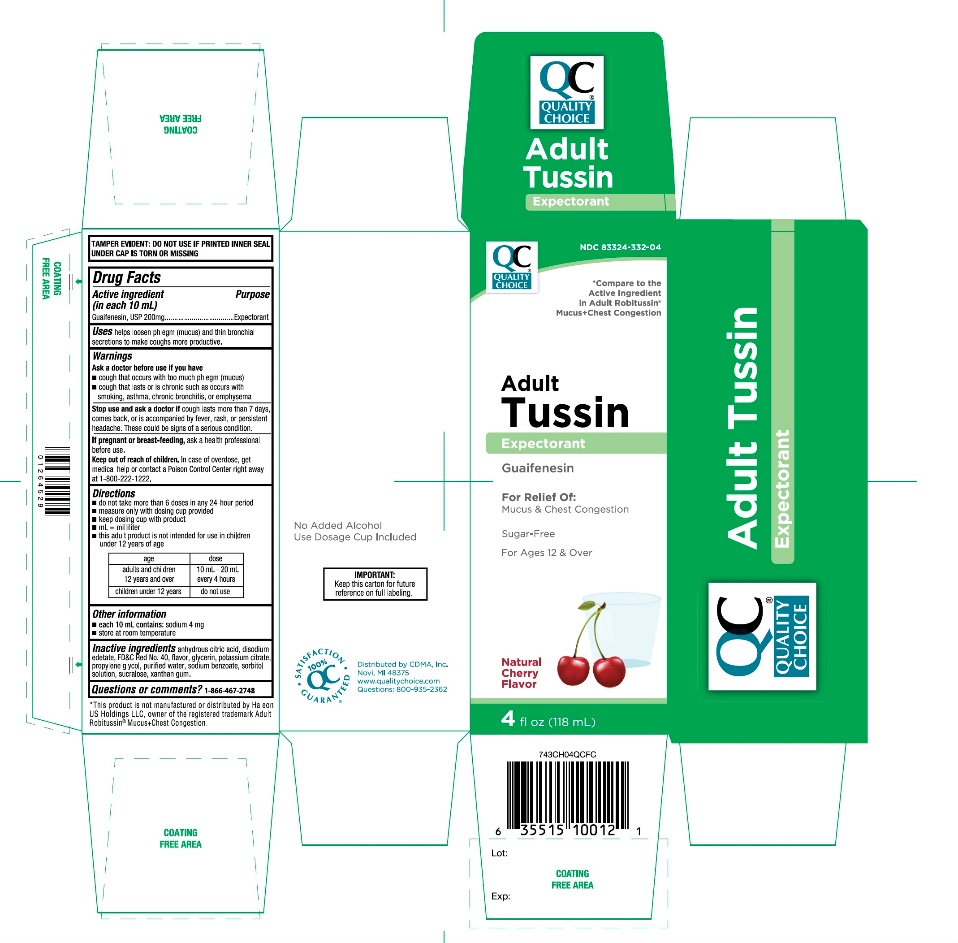 DRUG LABEL: QUALITY CHOICE

NDC: 83324-332 | Form: SYRUP
Manufacturer: QUALITY CHOICE (CHAIN DRUG MARKETING ASSOCIATION)
Category: otc | Type: HUMAN OTC DRUG LABEL
Date: 20250925

ACTIVE INGREDIENTS: GUAIFENESIN 200 mg/10 mL
INACTIVE INGREDIENTS: ANHYDROUS CITRIC ACID; EDETATE DISODIUM; FD&C RED NO. 40; GLYCERIN; POTASSIUM CITRATE; PROPYLENE GLYCOL; WATER; SODIUM BENZOATE; SORBITOL; SUCRALOSE; XANTHAN GUM

Quality Choice Adult Tussin Expectorant Drug Facts

Active ingredient (in each 10 mL)

Guaifenesin, USP 200 mg

Purpose

Expectorant

Uses

helps loosen phlegm (mucus) and thin bronchial secretions to make coughs more productive

Warnings

Ask a doctor before use if you have

- cough that occurs with too much phlegm (mucus)
- cough that lasts or is chronic such as occurs with smoking, asthma, chronic bronchitis, or emphysema

Stop use and ask a doctor if

cough lasts for more than 7 days, comes back, or is accompanied by fever, rash, or persistent headache. A persistent cough may be a sign of a serious condition.

If pregnant or breast-feeding,

ask a health professional before use.

Keep out of reach of children.

In case of overdose, get medical help or contact a Poison Control Center right away at 1-800-222-1222.

Directions

- do not take more than 6 doses in any 24-hour period
- measure only with dosing cup provided
- keep dosing cup with product
- mL = milliliter
- this adult product is not intended for use in children under 12 years of age

age | dose
adults and children 12 years and over | 10 ml – 20 ml every 4 hours
children under 12 years | do not use

Other information

- each 10 mL contains:sodium 4 mg
- store at room temperature

Inactive ingredients

anhydrous citric acid, disodium edetate, FD&C red no. 40, flavor, glycerin, potassium citrate, propylene glycol, purified water, sodium benzoate, sorbitol solution, sucralose, xanthan gum.

Questions or comments?

1-866-467-2748

Principal Display Panel

NDC# 83324-332-04

*Compare to the active ingredient in Adult Robitussin® Mucus+Chest Congestion

Quality Choice

ADULT

Tussin

Ecpectorant

Guaifenesin

For Relief of:

Mucus & Chest Congestion

Sugar-Free

For Ages 12 & Over

No Added Alcohol

Use Dosage Cup Included

Natural Cherry Flavor

4 FL OZ (118 mL)

TAMPER EVIDENT: DO NOT USE IF PRINTED INNER SEAL UNDER CAP IS TORN OR MISSING.

IMPORTANT:Keep this carton for future reference on full labeling.

Distributed by CDMA, Inc.

Novi, MI 48375

www.qualitychoice.com

Questions: 800-935-2362

*This product is not manufactured or distributed by Pfizer, owner of the registered trademark Adult Robitussin® Mucus + Chest Congestion.